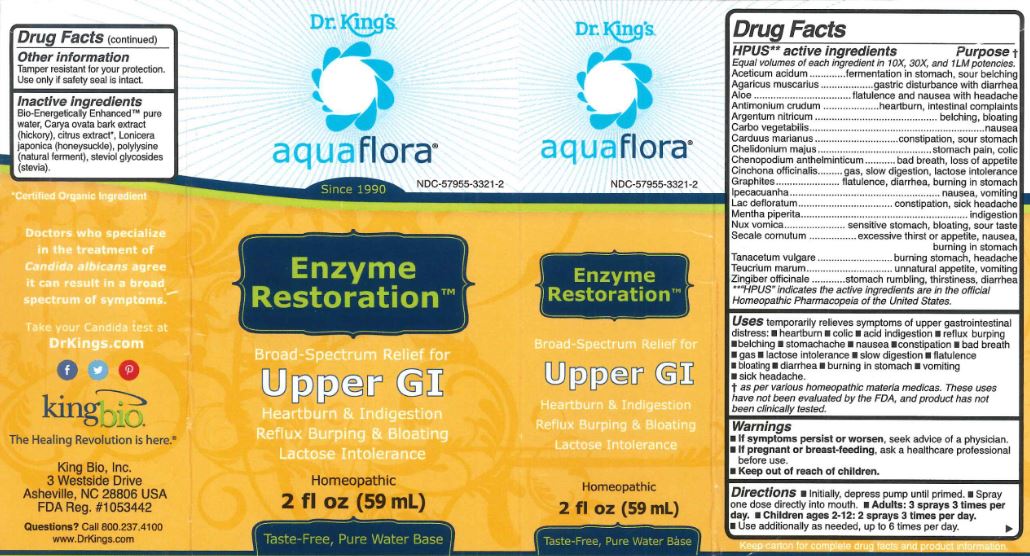 DRUG LABEL: Enzyme Restoration
NDC: 57955-3321 | Form: LIQUID
Manufacturer: King Bio Inc
Category: homeopathic | Type: HUMAN OTC DRUG LABEL
Date: 20180308

ACTIVE INGREDIENTS: ACETIC ACID 10 [hp_X]/59 mL; AMANITA MUSCARIA FRUITING BODY 10 [hp_X]/59 mL; ALOE 10 [hp_X]/59 mL; ANTIMONY TRISULFIDE 10 [hp_X]/59 mL; SILVER NITRATE 10 [hp_X]/59 mL; ACTIVATED CHARCOAL 10 [hp_X]/59 mL; MILK THISTLE 10 [hp_X]/59 mL; CHELIDONIUM MAJUS 10 [hp_X]/59 mL; DYSPHANIA AMBROSIOIDES 10 [hp_X]/59 mL; CINCHONA OFFICINALIS BARK 10 [hp_X]/59 mL; GRAPHITE 10 [hp_X]/59 mL; IPECAC 10 [hp_X]/59 mL; SKIM MILK 10 [hp_X]/59 mL; MENTHA PIPERITA 10 [hp_X]/59 mL; STRYCHNOS NUX-VOMICA SEED 10 [hp_X]/59 mL; CLAVICEPS PURPUREA SCLEROTIUM 10 [hp_X]/59 mL; TANACETUM VULGARE TOP 10 [hp_X]/59 mL; TEUCRIUM MARUM 10 [hp_X]/59 mL; GINGER 10 [hp_X]/59 mL
INACTIVE INGREDIENTS: WATER; CARYA OVATA BARK; CITRUS BIOFLAVONOIDS; LONICERA JAPONICA FLOWER; POLYEPSILON-LYSINE (4000 MW); REBAUDIOSIDE A

Enzyme Restoration

HPUS Active Ingredients

Aceticum acidum, Agaricus muscarius, Aloe, Antimonium crudum, Argentum nitricum, Carbo vegetabilis, Carduus marianus, Chelidonium majus, Chenopodium anthelminticum, Cinchona officinalis, Graphites, Ipecacuanha, Lac defloratum, Mentha piperita, Nux vomica, Secale cornutum, Tanacetum vulgare, Teucrium marum, Zingiber officinale

Uses

temporarily relieves symptoms of upper gastrointestinal distress:

- heartburn
- colic
- acid indigestion
- reflux burping
- belching
- stomachache
- nausea
- constipation
- bad breath
- gas
- lactose intolerance
- slow digestion
- flatulence
- bloating
- diarrhea
- burning in stomach
- vomiting
- sick headache

Directions

Intially, depress pump until primed.

Spray one dose directly into mouth.

Adults: 3 sprays 3 times per day.

Children ages 2-12: 2 sprays 3 times per day

Use additionally as needed, up to 6 times per day.

Warnings

If symptoms persist or worsen, seek advice of a physician.

If pregnant or breast-feeding, ask a healthcare professional before use.

Keep out of reach of children

Other Information

Tamper resistant for your protection. Use only if safety seal is intact.

Purpose

Aceticum acidum......fermentation in stomach, sour belching

Agaricus muscarius.....gastric disturbance with diarrhea

Aloe....flatulence and nausea with headache

Antimonium crudum....heartburn, intestinal complaints

Argentum nitricum........belching bloating

Carbo vegetabilis...........nausea

Carduus marianus.........constipation, sour stomach

Chelidonium majus.........stomach pain, colic

Chenopodium anthelminticum.......bad breath, loss of appetite

Cinchona officinalis............gas, slow digestion, lactose intolerances

Graphites..........flatulence, diarrhea, burning in stomach

Ipecacuanha.......nausea, vomiting

Lac defloratum.........constipation, sick headache

Mentha piperita.............indigestion

Nux vomica.......sensitive stomach, bloating, sour taste

Secale cornutum.............excessive thirst or appetite, nausea, burning in stoach

Tanacetum vulgare...........burning stomach, headache

Teucrium marum........unnatural appetite, vomiting

Zingiber officinale........stomach rumbling, thirstiness, diarrhea

Inactive Ingredients

Bio-Energetically EnhancedTM pure water, Carya ovata bark extract (hickory), citrus extract, Lonicera japonica(honeysuckle), polylysine (natural ferment), steviol glycosides (stevia).